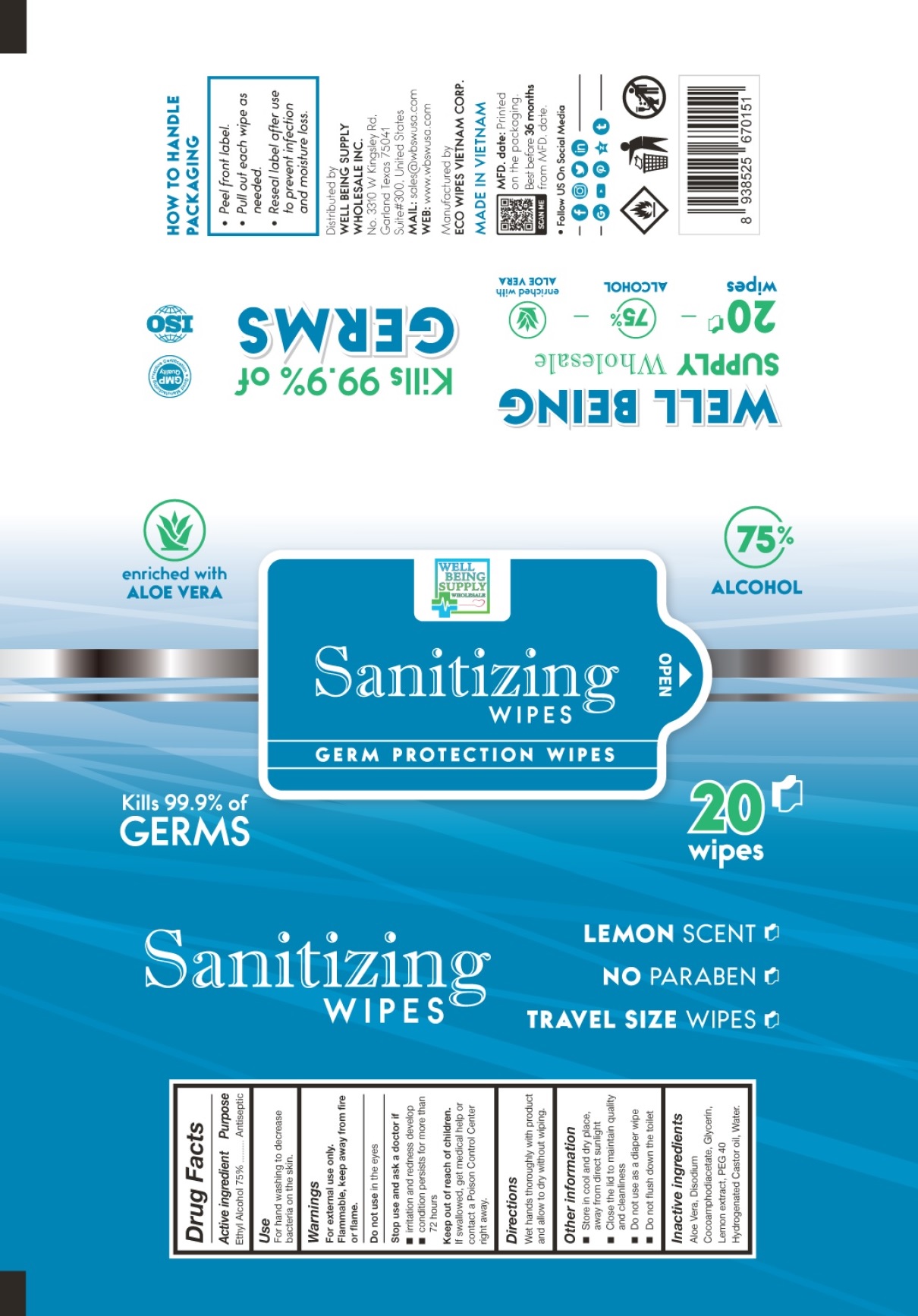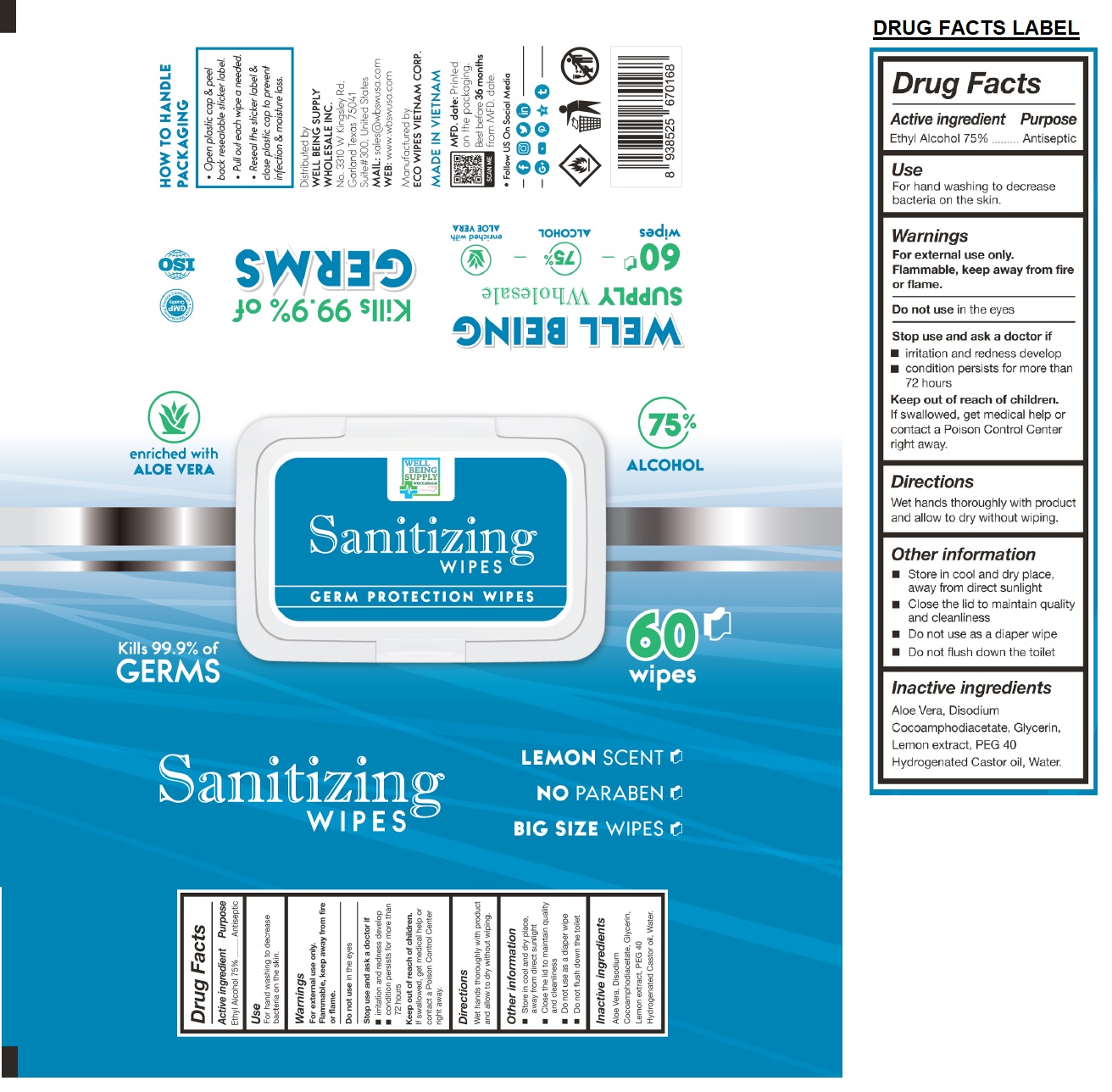 DRUG LABEL: WELL BEING SANITIZING WIPES
NDC: 78898-575 | Form: CLOTH
Manufacturer: Eco Wipes Vietnam Corporation
Category: otc | Type: HUMAN OTC DRUG LABEL
Date: 20200828

ACTIVE INGREDIENTS: ALCOHOL 75 mL/100 mL
INACTIVE INGREDIENTS: ALOE VERA LEAF; DISODIUM COCOAMPHODIACETATE; GLYCERIN; LEMON; POLYOXYL 40 HYDROGENATED CASTOR OIL; WATER

WELL BEING SUPPLY WHOLESALE Sanitizing WIPES

Active ingredient

Ethyl Alcohol 75%

Purpose

Antiseptic

Use

For hand washing to decrease bacteria on the skin.

Warnings

For external use only.

Flammable, keep away from fire or flame.

Do not use in the eyes

Stop use and ask a doctor if

• irritation and redness develop

• condition persists for more than 72 hours

Keep out of reach of children.

If swallowed, get medical help or contact a Poison Control Center right away.

Directions

Wet hands thoroughly with product and allow to dry without wiping.

Other information

• Store in cool and dry place away from direct sunlight

• Close the lid to maintain quality and cleanliness

• Do not use as a diaper wipe

• Do not flush down the toilet

Inactive ingredients

Aloe Vera, Disodium Cocoamphodiacetate, Glycerin, Lemon extract, PEG 40 Hydrogenated Castor oil, Water.

GERM PROTECTION WIPES

Kills 99.9% of GERMS

LEMON SCENT

NO PARABEN

TRAVEL SIZE WIPES

enriched with ALOE VERA

75% ALCOHOL

GMP Quality

Good Manufacturing Practices Certification

ISO

HOW TO HANDLE PACKAGING

• Peel front label.

• Pull out each wipe as needed.

• Reseal label after use to prevent infection and moisture loss.

Distributed by

WELL BEING SUPPLY WHOLESALE INC.

No. 3310 W Kingsley Rd.

Garland Texas 75041

Suite#300, United States

MAIL: sales@wbswusa.com

WEB: www.wbswusa.com

Manufactured by

ECO WIPES VIETNAM CORP.

MADE IN VIETNAM

MFD. date: Printed on the packaging

Best before 36 MONTHS from MFD date.

• Follow US On Social Media